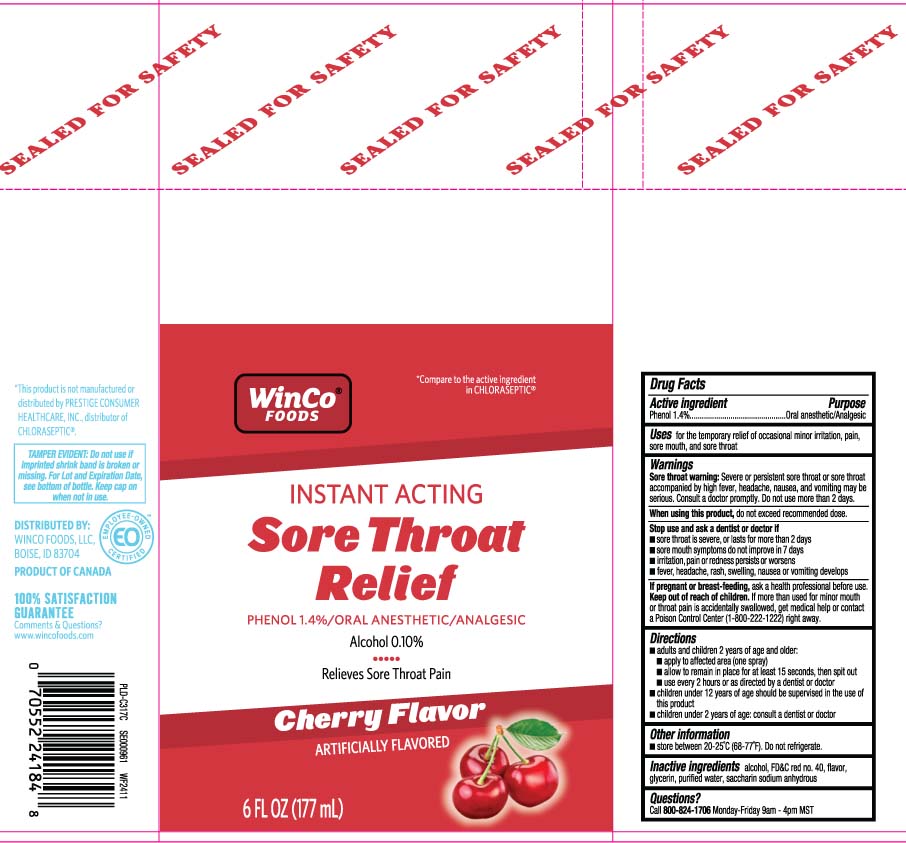 DRUG LABEL: Sore Throat Relief
NDC: 67091-267 | Form: SPRAY
Manufacturer: WinCo Foods, LLC
Category: otc | Type: HUMAN OTC DRUG LABEL
Date: 20241120

ACTIVE INGREDIENTS: PHENOL 1.4 g/100 mL
INACTIVE INGREDIENTS: ALCOHOL; FD&C RED NO. 40; GLYCERIN; WATER; SACCHARIN SODIUM

Drug Facts

Active ingredient

Phenol 1.4%

Purpose

Oral Anesthetic/Analgesic

Uses

temporarily relieves sore throat pain, sore mouth, pain associated with canker sores, minor mouth irritation

Warnings

Sore throat warning: Severe or persistent sore throat or sore throat accompanied by high fever, headache, nausea, and vomiting may be serious. Consult a doctor promptly. Do not use more than 2 days.

When using this product,

do not exceed recommended dose.

Stop use and ask a dentist or doctor if

- sore throat is severe, or last for more than 2 days
- sore mouth symptoms do not improve in 7 days
- irritation, pain or redness persists or worsen
- fever, headache, rash, swelling, nausea or vomiting develops

If pregnant or breast-feeding,

ask a health professional before use.

Keep out of reach of children.

If more than used for minor mouth or throat pain is accidentally swallowed, get medical help or contact a Poison Control Center (1-800-222-1222) right away.

Directions

- adults and children 2 years of age and older:
  - apply to affected area (one spray)
  - allow to remain in place for at least 15 seconds, then spit out
  - use every 2 hours or as directed by a dentist or doctor
- children under 12 years of age should be supervised in the use of this product
- children under 2 years of age: consult a dentist or doctor

Other information

- store between 20º-25ºC (68º-77ºF). Do not refrigerate.

Inactive ingredients

alcohol, FD&C red #40, flavor, glycerin, purified water, saccharin sodium anhydrous

Questions?

Call 800-824-1706 Monday-Friday 9am-4pm MST

Principal Display Panel

*Compare to the active ingredient in Chloraseptic®

INSTANT ACTING

Sore Throat Relief

PHENOL 1.4%/ORAL ANESTHETIC/ANALGESIC

Alcohol 0.10%

Relieves Sore Throat Pain

Cherry Flavor

ARTIFICALLY FLAVORED

FL OZ (mL)

*This product is not manufactured or distributed by PRESTIGE CONSUMER HEALTHCARE, INC., distributor of CHLORASEPTIC®.

TAMPER EVIDENT: Do not use if imprinted shrink band is broken or missing. For Lot and Expiration Date, see bottom of bottle. Keep cap on when not is use.

DISTRIBUTED BY:

WINCO FOODS LLC

BOISE, ID 83704

Package Label

WINCO FOODS Sore Throat Relief Cherry Flavor